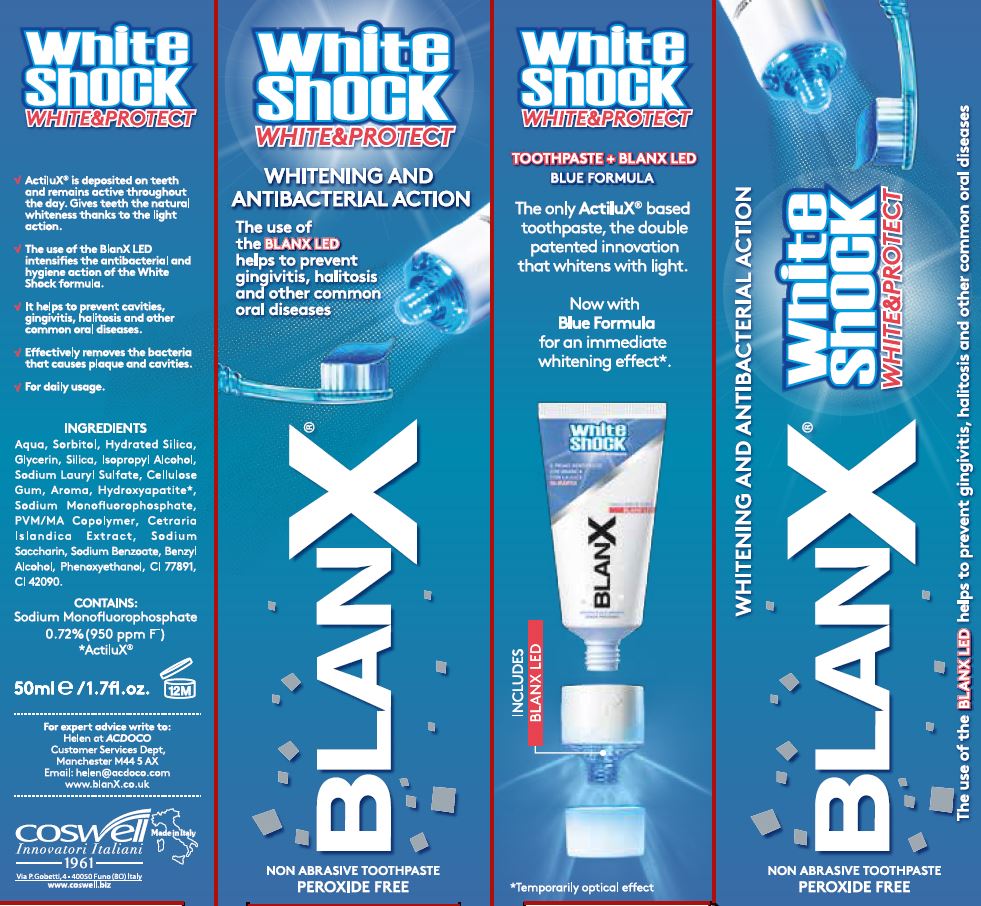 DRUG LABEL: BlanX White Shock White and Protect
NDC: 70781-005 | Form: PASTE
Manufacturer: Coswell Spa
Category: otc | Type: HUMAN OTC DRUG LABEL
Date: 20190204

ACTIVE INGREDIENTS: SODIUM MONOFLUOROPHOSPHATE 0.4 g/100 g
INACTIVE INGREDIENTS: COPOVIDONE; SILICON DIOXIDE; TITANIUM DIOXIDE; BENZYL ALCOHOL; PHENOXYETHANOL; SACCHARIN SODIUM; SODIUM BENZOATE; CARBOXYMETHYLCELLULOSE SODIUM; GLYCERIN; CETRARIA ISLANDICA SUBSP. ISLANDICA; WATER; SORBITOL; HYDRATED SILICA; ISOPROPYL ALCOHOL; SODIUM LAURYL SULFATE; FD&C BLUE NO. 1; TRIBASIC CALCIUM PHOSPHATE

BlanX White Shock White and Protect

ACTIVE INGREDIENT

Contains:

Sodium Monofluorophosphate 0.72% (950ppm F)

*ActiluX®

INACTIVE INGREDIENT

Ingredients:

Aqua, Sorbitol, Hydrated Silica, Glycerin, Silica, Isopropyl Alcohol, Sodium Lauryl Sulfate, Cellulose Gum, Aroma, Hydroxyapatite*, Sodium Monofluorophosphate, PVM/MA Copolymer, Cetraria Islandica Extract, Sodium Saccharin, Sodium Benzoate, Phenoxyethanol, Benzyl Alcohol, Phenoxyethanol, CI 77891, CI 42090.

PURPOSE

Whitening and Antibacterial Action

The use of the BLANX LED helps to prevent gingivitis, halitosis and other common oral diseases

The only ActiluX® based toothpaste, the double patented innovation that whitens with light.

Now with Blue Formula for an immediate whitening effect*.

ActiluX® is deposited on teeth and remains active throughout the day. Gives teeth the natural whiteness thanks to the light action.

The use of the BlanX LED intensifies the antibacterial and hygiene action of the White Shock formula.

It helps to prevent cavities, gingivitis, halitosis and other common oral diseases.

Effectively removes the bacteria that causes plaque and cavities.

Keep out of reach of children

DOSAGE AND ADMINISTRATION

For daily usage.

For daily usage.

Warnings